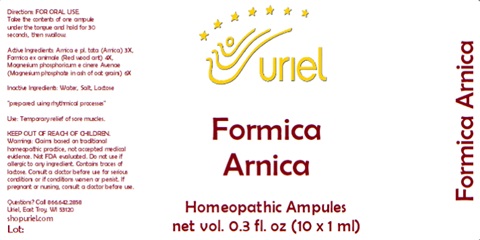 DRUG LABEL: Formica Arnica
NDC: 48951-4086 | Form: LIQUID
Manufacturer: Uriel Pharmacy Inc.
Category: homeopathic | Type: HUMAN OTC DRUG LABEL
Date: 20240126

ACTIVE INGREDIENTS: ARNICA MONTANA 3 [hp_X]/1 mL; FORMICA RUFA 4 [hp_X]/1 mL; MAGNESIUM PHOSPHATE, TRIBASIC, PENTAHYDRATE 6 [hp_X]/1 mL
INACTIVE INGREDIENTS: SODIUM CHLORIDE; LACTOSE; WATER

Formica Arnica

INDICATIONS AND USAGE

Directions: FOR ORAL USE.

DOSAGE AND ADMINISTRATION

Take the contents of one ampule under the tongue and hold for 30 seconds, then swallow.

ACTIVE INGREDIENT

Active Ingredients: Arnica e pl. tota (Arnica) 3X, Formica ex animale (Red wood ant) 4X, Magnesium phosphoricum e cinere Avenae (Magnesium phosphate in ash of oat grains) 6X

Inactive Ingredients: Water, Salt, Lactose

"prepared using rhythmical processes"

PURPOSE

Use: Temporary relief of sore muscles.

KEEP OUT OF REACH OF CHILDREN.

WARNINGS

Warnings: Claims based on traditional homeopathic practice, not accepted medical evidence. Not FDA evaluated. Do not use if allergic to any ingredient. Contains traces of lactose. Consult a doctor before use for serious conditions or if conditions worsen or persist. If pregnant or nursing, consult a doctor before use.

QUESTIONS

Questions? Call 866.642.2858 Uriel, East Troy, WI 53120 shopuriel.com Lot: